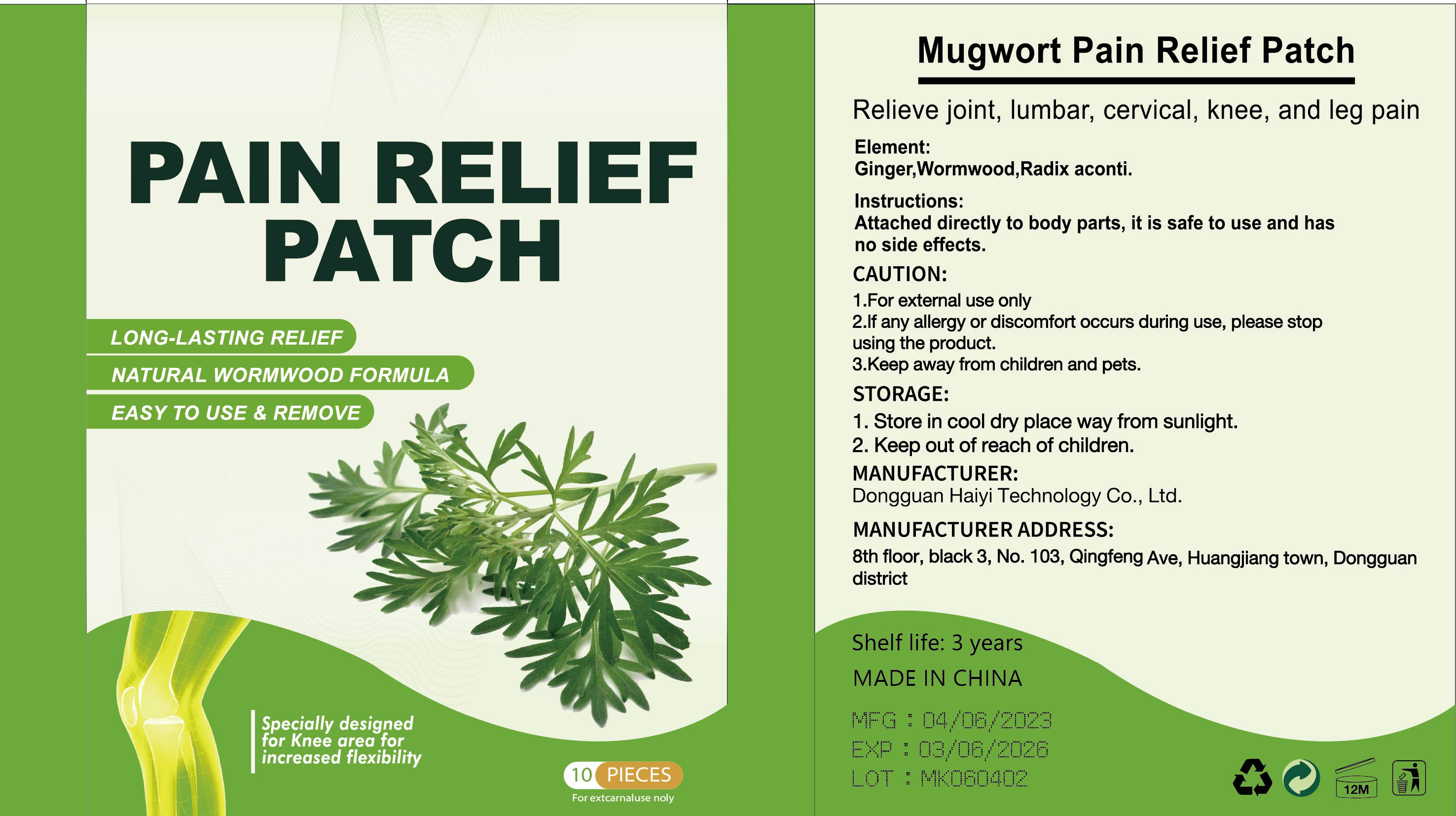 DRUG LABEL: Mugwort Pain Relief Patch
NDC: 84732-092 | Form: PATCH
Manufacturer: Dongguan Haiyi Technology Co.,Ltd.
Category: otc | Type: HUMAN OTC DRUG LABEL
Date: 20241117

ACTIVE INGREDIENTS: GINGER 1 mg/100 g
INACTIVE INGREDIENTS: ACONITUM NAPELLUS ROOT; WORMWOOD

Active ingredient

Ginger

Inactive ingredient

Wormwood,Radix aconti.

Purpose section

Relieve joint, lumbar, cervical, knee, and leg pain

Warning

1.For external use only.

2.lf any allergy or discomfort occurs during use, please stopusing the product.

3.Keep away from children and pets.

stop use

lf any allergy or discomfort occurs during use, please stop using the product.

not use

Not suitable for use by children, pregnantor breast feeding people.

OUT OF CHILDREN

KEEP THE PRODUCT OUT OF REACH OF CHILDREN to

HOW TO USE

Attached directly to body parts, it is safe to use and has no side effects.

Dosage

take an appropriateamount,Use 2-3 times a week